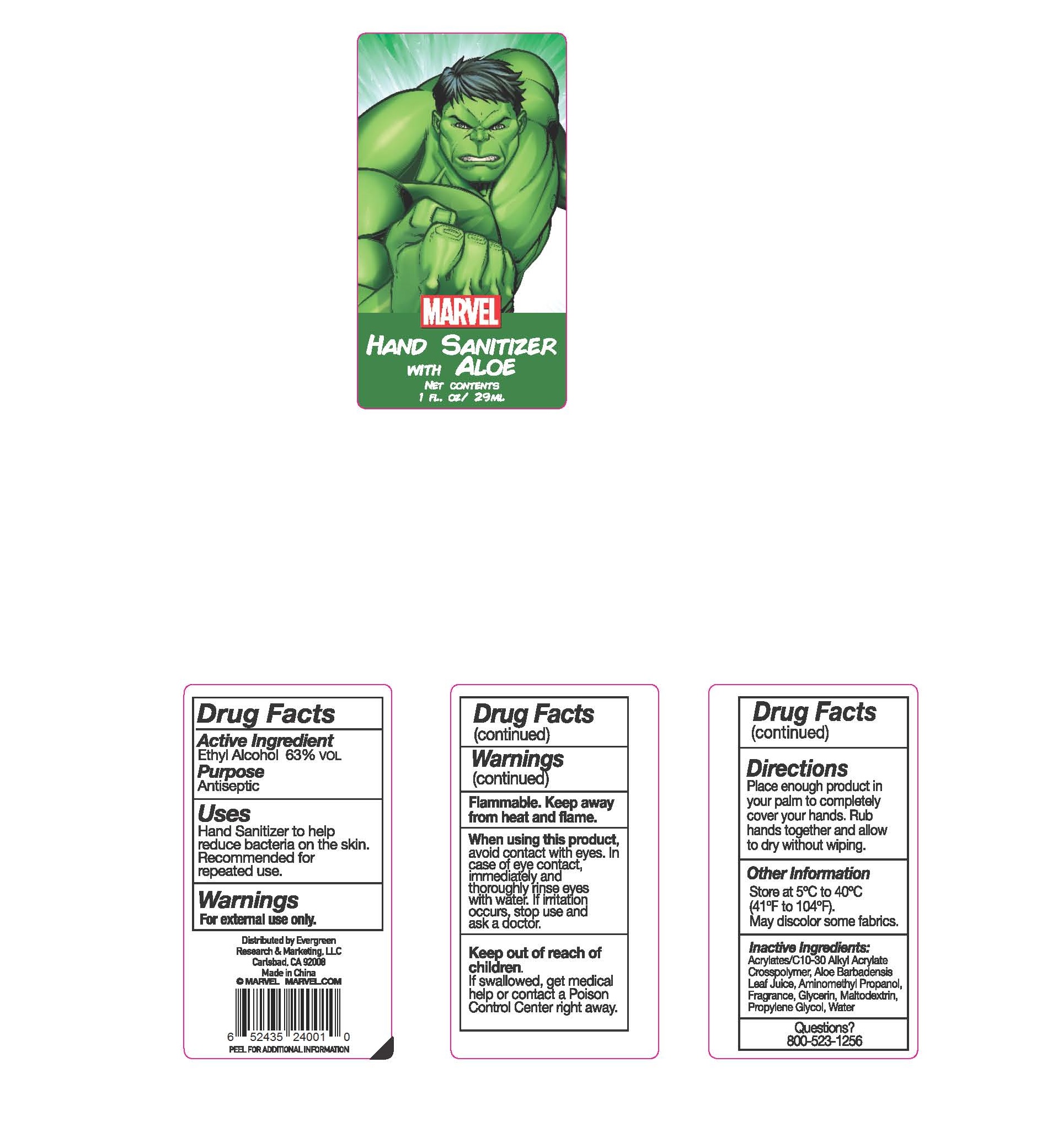 DRUG LABEL: Hand Sanitizer with Aloe
NDC: 70424-003 | Form: GEL
Manufacturer: Evergreen Research and Marketing, LLC
Category: otc | Type: HUMAN OTC DRUG LABEL
Date: 20170531

ACTIVE INGREDIENTS: ALCOHOL 63 mL/100 mL
INACTIVE INGREDIENTS: MALTODEXTRIN; WATER; ALOE VERA LEAF; GLYCERIN; PROPYLENE GLYCOL; CARBOMER COPOLYMER TYPE A (ALLYL PENTAERYTHRITOL CROSSLINKED); AMINOMETHYL PROPANEDIOL

Active Ingredient:
Ethyl Alcohol 63% VOL

Purpose

Antiseptic

Warnings

For external use only.

Flammable. Keep away from heat and flame.

STOP USE

If irritation occurs, stop use and ask a doctor.

Keep out of reach of children.

If swallowed, get medical help or contact a Poison Control Center right away.

Directions:

Place enough product in your palm to completely cover your hands. Rub hands together and allow to dry without wiping.

Inactive Ingredients:

Acrylates/C10-30 Alkyl Acrylate Crosspolymer, Aloe Barbadensis Leaf Juice, Aminomethyl Propanol, Fragrance, Glycerin, Maltodextrin, Propylene Glycol, Water

Other Information

Store at 5C to 40C (41F to 104F). May discolor some fabrics.

Uses

Hand sanitizer to help reduce bacteria on the skin. Recommended for repeated use.

When using this product

Avoid contact with eyes. In case of eye contact, immediately and thoroughly rinse eyes with water.